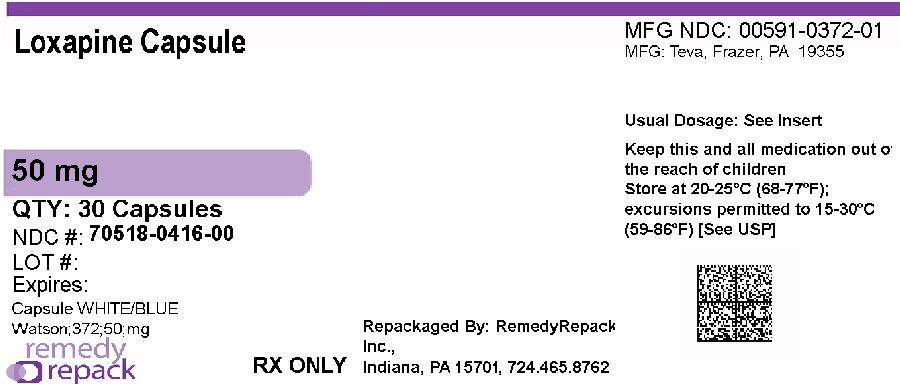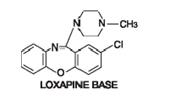 DRUG LABEL: Loxapine
NDC: 70518-0416 | Form: CAPSULE
Manufacturer: REMEDYREPACK INC.
Category: prescription | Type: HUMAN PRESCRIPTION DRUG LABEL
Date: 20260218

ACTIVE INGREDIENTS: LOXAPINE SUCCINATE 50 mg/1 1
INACTIVE INGREDIENTS: AMMONIA; ANHYDROUS LACTOSE; BENZYL ALCOHOL; BUTYLPARABEN; EDETATE CALCIUM DISODIUM; FD&C BLUE NO. 1; FERROSOFERRIC OXIDE; GELATIN; MAGNESIUM STEARATE; METHYLPARABEN; POLACRILIN POTASSIUM; POTASSIUM HYDROXIDE; PROPYLENE GLYCOL; PROPYLPARABEN; SHELLAC; SODIUM LAURYL SULFATE; SODIUM PROPIONATE; TALC; TITANIUM DIOXIDE

Loxapine capsules A072062 A072204 A072205 A072206

Loxapine Capsules, USP

Rx only

WARNING

Increased Mortality in Elderly Patients with Dementia-Related Psychosis

Elderly patients with dementia-related psychosis treated with antipsychotic drugs are at an increased risk of death. Analyses of seventeen placebo-controlled trials (modal duration of 10 weeks), largely in patients taking atypical antipsychotic drugs, revealed a risk of death in drug-treated patients of between 1.6 to 1.7 times the risk of death in placebo-treated patients. Over the course of a typical 10-week controlled trial, the rate of death in drug-treated patients was about 4.5%, compared to a rate of about 2.6% in the placebo group. Although thecauses of death were varied, most of the deaths appearedto be either cardiovascular (e.g., heart failure, sudden death) or infectious (e.g., pneumonia) in nature. Observational studies suggest that, similar to atypical antipsychotic drugs, treatment with conventional antipsychotic drugs may increase mortality. The extent to which the findings of increased mortality in observational studies may be attributed to the antipsychotic drug as opposed to some characteristic(s) of the patients is not clear. Loxapine is not approved for the treatment of patients with dementia-related psychosis(see WARNINGS).

DESCRIPTION

Loxapine, a dibenzoxazepine compound, represents a subclass of tricyclic antipsychotic agents, chemically distinct from the thioxanthenes, butyrophenones, and phenothiazines. Chemically, it is 2-Chloro-11-(4-methyl-1-piperazinyl)dibenz[ b,f][1,4]oxazepine. It is present as the succinate salt.

Each capsule for oral administration, contains loxapine succinate, USP 6.8 mg, 13.6 mg, 34.0 mg or 68.1 mg equivalent to 5 mg, 10 mg, 25 mg or 50 mg of loxapine base respectively. It also contains the following inactive ingredients: anhydrous lactose, benzyl alcohol, butyl paraben, edetate calcium disodium, gelatin, magnesium stearate, methyl paraben, polacrilin potassium, propyl paraben, sodium lauryl sulfate, sodium propionate, talc, and titanium dioxide. The printing ink contains black iron oxide, propylene glycol, potassium hydroxide, shellac, strong ammonia solution. Additionally, the 10 mg capsule contains D&C Yellow No. 10 and FD&C Yellow No. 6, the 25 mg capsule contains D&C Yellow No. 10 and FD&C Blue No. 1, and the 50 mg capsule contains FD&C Blue No. 1.

CLINICALPHARMACOLOGY

Pharmacodynamics:

Pharmacologically, loxapine is an antipsychotic for which the exact mode of action has not been established. However, changes in the level of excitability of subcortical inhibitory areas have been observed in several animal species in association with such manifestations of tranquilization as calming effects and suppression of aggressive behavior.

In normal human volunteers, signs of sedation were seen within 20 to 30 minutes after administration, were most pronounced within one and one-half to three hours, and lasted through 12 hours. Similar timing of primary pharmacologic effects was seen in animals.

Absorption, Distribution, Metabolism, and Excretion

Absorption of loxapine following oral administration is virtually complete. The drug is removed rapidly from the plasma and distributed in tissues. Animal studies suggest an initial preferential distribution in lungs, brain, spleen, heart, and kidney. Loxapine is metabolized extensively and is excreted mainly in the first 24 hours. Metabolites are excreted in the urine in the form of conjugates and in the feces unconjugated.

INDICATIONS AND USAGE

Loxapine capsules are indicated for the treatment of schizophrenia. The efficacy of loxapine in schizophrenia was established in clinical studies which enrolled newly hospitalized and chronically hospitalized acutely ill schizophrenic patients as subjects.

CONTRAINDICATIONS

Loxapine is contraindicated in comatose or severe drug-induced depressed states (alcohol, barbiturates, narcotics, etc.).

Loxapine is contraindicated in individuals with known hypersensitivity to dibenzoxazepines.

WARNINGS

Increased Mortality in Elderly Patients with Dementia-Related Psychosis
Elderly patients with dementia-related psychosis treated with antipsychotic drugs are at an increased risk of death. Loxapine is not approved for the treatment of patients with dementia-related psychosis(see BOXED WARNING).

Tardive Dyskinesia

Tardive dyskinesia, a syndrome consisting of potentially irreversible, involuntary, dyskinetic movements, may develop in patients treated with antipsychotic drugs. Although the prevalence of the syndrome appears to be highest among the elderly, especially elderly women, it is impossible to rely upon prevalence estimates to predict, at the inception of antipsychotic treatment, which patients are likely to develop the syndrome. Whether antipsychotic drug products differ in their potential to cause tardive dyskinesia is unknown.

Both the risk of developing the syndrome and the likelihood that it will become irreversible are believed to increase as the duration of treatment and the total cumulative dose of antipsychotic drugs administered to the patient increase. However, the syndrome can develop, although much less commonly, after relatively brief treatment periods at low doses.

There is no known treatment for established cases of tardive dyskinesia, although the syndrome may remit, partially or completely, if antipsychotic treatment is withdrawn. Antipsychotic treatment itself, however, may suppress (or partially suppress) the signs and symptoms of the syndrome and thereby may possibly mask the underlying disease process. The effect that symptomatic suppression has upon the long-term course of the syndrome is unknown.

Given these considerations, antipsychotics should be prescribed in a manner that is most likely to minimize the occurrence of tardive dyskinesia. Chronic antipsychotic treatment should generally be reserved for patients who suffer from a chronic illness that, 1) is known to respond to antipsychotic drugs, and 2) for whom alternative, equally effective, but potentially less harmful treatments are notavailable or appropriate. In patients who do require chronic treatment, the smallest dose and the shortest duration of treatment producing a satisfactory clinical response should be sought. The need for continued treatment should be reassessed periodically.

If signs and symptoms of tardive dyskinesia appear in a patient on antipsychotics, drug discontinuation should be considered. However, some patients may require treatment despite the presence of the syndrome. (See ADVERSE REACTIONS and Information for Patients sections.)

Neuroleptic Malignant Syndrome (NMS)

A potentially fatal symptom complex sometimes referred to as Neuroleptic Malignant Syndrome (NMS) has been reported in association with antipsychotic drugs. Clinical manifestations of NMS are hyperpyrexia, muscle rigidity, altered mental status, and evidence of autonomic instability (irregular pulse or blood pressure, tachycardia, diaphoresis, and cardiac dysrhythmias).

The diagnostic evaluation of patients with this syndrome is complicated. In arriving at a diagnosis, it is important to identify cases where the clinical presentation includes both serious medical illness (e.g., pneumonia, systemic infection, etc.) and untreated or inadequately treated extrapyramidal signs and symptoms (EPS). Other important considerations in the differential diagnosis include central anticholinergic toxicity, heat stroke, drug fever, and primary central nervous system (CNS) pathology.

The management of NMS should include: 1) immediate discontinuation of antipsychotic drugs and other drugs not essential to concurrent therapy, 2) intensive symptomatic treatment and medical monitoring, and 3) treatment of any concomitant serious medical problems for which specific treatments are available. There is no general agreement about specific pharmacological treatment regimens for uncomplicated NMS.

If a patient requires antipsychotic drug treatment after recovery from NMS, the potential reintroduction of drug therapy should be carefully considered. The patient should be carefully monitored, since recurrences of NMS have been reported.

Loxapine, like other antipsychotics, may impair mental and/or physical abilities, especially during the first few days of therapy. Therefore, ambulatory patients should be warned about activities requiring alertness (e.g., operating vehicles or machinery) and about concomitant use of alcohol and other CNS depressants.

Loxapine has not been evaluated for the management of behavioral complications in patients with mental retardation, and therefore, it cannot be recommended.

Falls

Loxapine may cause somnolence, postural hypotension, motor and sensory instability, which may lead to falls and, consequently, fractures or other injuries. For patients with diseases, conditions, or medications that could exacerbate these effects, complete fall risk assessments when initiating antipsychotic treatment and recurrently for patients on long-term antipsychotic therapy.

PRECAUTIONS

Leukopenia, Neutropenia and Agranulocytosis

In clinical trial and postmarketing experience, events of leukopenia/neutropenia and agranulocytosis have been reported temporally related to antipsychotic agents.

Possible risk factors for leukopenia/neutropenia include preexisting low white blood cell count (WBC) and history of drug induced leukopenia/neutropenia. Patients with a preexisting low WBC or a history of drug induced leukopenia/neutropenia should have their complete blood count (CBC) monitored frequently during the first few months of therapy and should discontinue loxapine succinate capsules at the first sign of a decline in WBC in the absence of other causative factors.

Patients with neutropenia should be carefully monitored for fever or other symptoms or signs of infection and treated promptly if such symptoms or signs occur. Patients with severe neutropenia (absolute neutrophil count <1000/mm^3) should discontinue loxapine succinate capsules and have their WBC followed until recovery.

General

Loxapine should be used with extreme caution in patients with a history of convulsive disorders since it lowers the convulsive threshold. Seizures have been reported in patients receiving loxapine at antipsychotic dose levels, and may occur in epileptic patients even with maintenance of routine anticonvulsant drug therapy.

Loxapine has an antiemetic effect in animals. Since this effect may also occur in man, loxapine may mask signs of overdosage of toxic drugs and may obscure conditions such as intestinal obstruction and brain tumor.

Loxapine should be used with caution in patients with cardiovascular disease. Increased pulse rates have been reported in the majority of patients receiving antipsychotic doses; transient hypotension has been reported. In the presence of severe hypotension requiring vasopressor therapy, the preferred drugs may be norepinephrine or angiotensin. Usual doses of epinephrine may be ineffective because of inhibition of its vasopressor effect by loxapine.

The possibility of ocular toxicity from loxapine cannot be excluded at this time. Therefore, careful observation should be made for pigmentary retinopathy and lenticular pigmentation since these have been observed in some patients receiving certain other antipsychotic drugs for prolonged periods.

Because of possible anticholinergic action, the drug should be used cautiously in patients with glaucoma or a tendency to urinary retention, particularly with concomitant administration of anticholinergic-type antiparkinson medication.

Experience to date indicates the possibility of a slightly higher incidence of extrapyramidal effects following intramuscular administration than normally anticipated with oral formulations. The increase may be attributable to higher plasma levels following intramuscular injection.

Antipsychotic drugs elevate prolactin levels; the elevation persists during chronic administration. Tissue culture experiments indicate that approximately one-third of human breast cancers are prolactin-dependent in vitro,a factor of potential importance if the prescription of these drugs is contemplated in a patient with a previously detected breast cancer. Although disturbances such as galactorrhea, amenorrhea, gynecomastia, and impotence have been reported, the clinical significance of elevated serum prolactin levels is unknown for most patients. An increase in mammary neoplasms has been found in rodents after chronic administration of antipsychotic drugs. Published epidemiologic studies have shown inconsistent results when exploring the potential association between hyperprolactinemia and breast cancer.

Information for Patients

Given the likelihood that some patients exposed chronically to antipsychotics will develop tardive dyskinesia, it is advised that all patients in whom chronic use is contemplated be given, if possible, full information about this risk. The decision to inform patients and/or their guardians must obviously take into account the clinical circumstances and the competency of the patient to understand the information provided.

Repackaged By / Distributed By: RemedyRepack Inc.

625 Kolter Drive, Indiana, PA 15701

(724) 465-8762

Drug Interactions

There have been rare reports of significant respiratory depression, stupor and/or hypotension with the concomitant use of loxapine and lorazepam.

The risk of using loxapine in combination with CNS-active drugs has not been systematically evaluated. Therefore, caution is advised if the concomitant administration of loxapine and CNS-active drugs is required.

Pregnancy

Non-teratogenic Effects
Neonates exposed to antipsychotic drugs, during the third trimester of pregnancy are at risk for extrapyramidal and/or withdrawal symptoms following delivery. There have been reports of agitation, hypertonia, hypotonia, tremor, somnolence, respiratory distress and feeding disorder in these neonates. These complications have varied in severity; while in some cases symptoms have been self-limited, in other cases neonates have required intensive care unit support and prolonged hospitalization.

Loxapine succinate should be used during pregnancy only if the potential benefit justifies the potential risk to the fetus.

Safe use of loxapine during pregnancy or lactation has not been established; therefore, its use in pregnancy, in nursing mothers, or in women of childbearing potential requires that the benefits of treatment be weighed against the possible risks to mother and child. No embryotoxicity or teratogenicity was observed in studies in rats, rabbits, or dogs although, with the exception of one rabbit study, the highest dosage was only two times the maximum recommended human dosage and in some studies it was below this dose. Perinatal studies have shown renal papillary abnormalities in offspring of rats treated from mid-pregnancy with doses of 0.6 and 1.8 mg/kg, doses which approximate the usual human dose but which are considerably below the maximum recommended human dose.

Nursing Mothers

The extent of the excretion of loxapine or its metabolites in human milk is not known. However, loxapine and its metabolites have been shown to be transported into the milk of lactating dogs. Loxapine administration to nursing women should be avoided if clinically possible.

Pediatric Use

Safety and effectiveness of loxapine in pediatric patients have not been established.

ADVERSE REACTIONS

CNS Effects:Manifestations of adverse effects on the central nervous system, other than extrapyramidal effects, have been seen infrequently. Drowsiness, usually mild, may occur at the beginning of therapy or when dosage is increased. It usually subsides with continued loxapine therapy. The incidence of sedation has been less than that of certain aliphatic phenothiazines and slightly more than the piperazine phenothiazines. Dizziness, faintness, staggering gait, shuffling gait, muscle twitching, weakness, insomnia, agitation, tension, seizures, akinesia, slurred speech, numbness, and confusional states have been reported. Neuroleptic malignant syndrome (NMS) has been reported (see WARNINGS).

Extrapyramidal Symptoms - Neuromuscular (extrapyramidal) reactions during the administration of loxapine have been reported frequently, often during the first few days of treatment. In most patients, these reactions involved parkinsonian-like symptoms such as tremor, rigidity, excessive salivation, and masked facies. Akathisia (motor restlessness) also has been reported relatively frequently. These symptoms are usually not severe and can be controlled by reduction of loxapine dosage or by administration of antiparkinson drugs in usual dosage.

Dystonia- Class effect:Symptoms of dystonia, prolonged abnormal contractions of muscle groups, may occur in susceptible individuals during the first few days of treatment. Dystonic symptoms include: spasm of the neck muscles, sometimes progressing to tightness of the throat, swallowing difficulty, difficulty breathing, and/or protrusion of the tongue. While these symptoms can occur at low doses, they occur more frequently and with greater severity with high potency and at higher doses of first generation antipsychotic drugs. An elevated risk of acute dystonia is observed in males and younger age groups.

Persistent Tardive Dyskinesia - As with all antipsychotic agents, tardive dyskinesia may appear in some patients on long-term therapy or may appear after drug therapy has been discontinued. The risk appears to be greater in elderly patients on high-dose therapy, especially females. The symptoms are persistent and in some patients appear to be irreversible. The syndrome is characterized by rhythmical involuntary movement of the tongue, face, mouth or jaw (e.g., protrusion of tongue, puffing of cheeks, puckering of mouth, chewing movements). Sometimes these may be accompanied by involuntary movements of extremities.

There is no known effective treatment for tardive dyskinesia; antiparkinson agents usually do not alleviate the symptoms of this syndrome. It is suggested that all antipsychotic agents be discontinued if these symptoms appear. Should it be necessary to reinstitute treatment, or increase the dosage of the agent, or switch to a different antipsychotic agent, the syndrome may be masked. It has been suggested that fine vermicular movements of the tongue may be an early sign of the syndrome, and if the medication is stopped at that time the syndrome may not develop.

Cardiovascular Effects:Tachycardia, hypotension, hypertension, orthostatic hypotension, lightheadedness, and syncope have been reported.

A few cases of ECG changes similar to those seen with phenothiazines have been reported. It is not known whether these were related to loxapine administration.

Hematologic:Rarely, agranulocytosis, thrombocytopenia, leukopenia.

Skin:Dermatitis, edema (puffiness of face), pruritus, rash, alopecia, and seborrhea have been reported with loxapine.

Anticholinergic Effects:Dry mouth, nasal congestion, constipation, blurred vision, urinary retention, and paralytic ileus have occurred.

Gastrointestinal:Nausea and vomiting have been reported in some patients. Hepatocellular injury (i.e., SGOT/SGPT elevation) has been reported in association with loxapine administration and rarely, jaundice and/or hepatitis questionably related to loxapine treatment.

Other Adverse Reactions:Weight gain, weight loss, dyspnea, ptosis, hyperpyrexia, flushed facies, headache, paresthesia, and polydipsia have been reported in some patients. Rarely, galactorrhea, amenorrhea, gynecomastia, and menstrual irregularity of uncertain etiology have been reported.

To report SUSPECTED ADVERSE REACTIONS, contact Teva at 1-888-838-2872 or FDA at 1-800-FDA-1088 or www.fda.gov/medwatch.

OVERDOSAGE

Signs and symptoms of overdosage will depend on the amount ingested and individual patient tolerance. As would be expected from the pharmacologic actions of the drug, the clinical findings may range from mild depression of the CNS and cardiovascular systems to profound hypotension, respiratory depression, and unconsciousness. The possibility of occurrence of extrapyramidal symptoms and/or convulsive seizures should be kept in mind. Renal failure following loxapine overdosage has also been reported.

The treatment of overdosage is essentially symptomatic and supportive. Early gastric lavage and extended dialysis might be expected to be beneficial. Centrally-acting emetics may have little effect because of the antiemetic action of loxapine. In addition, emesis should be avoided because of the possibility of aspiration of vomitus. Avoid analeptics, such as pentylenetetrazol, which may cause convulsions. Severe hypotension might be expected to respond to the administration of norepinephrine or phenylephrine. EPINEPHRINE SHOULD NOT BE USED SINCE ITS USE IN A PATIENT WITH PARTIAL ADRENERGIC BLOCKADE MAY FURTHER LOWER THE BLOOD PRESSURE.Severe extrapyramidal reactions should be treated with anticholinergic antiparkinson agents or diphenhydramine hydrochloride, and anticonvulsant therapy should be initiated as indicated. Additional measures include oxygen and intravenous fluids.

DOSAGE AND ADMINISTRATION

Loxapine capsules are administered, usually in divided doses, two to four times a day. Daily dosage (in terms of base equivalents) should be adjusted to the individual patient’s needs as assessed by the severity of symptoms and previous history of response to antipsychotic drugs.

Oral Administration

Initial dosage of 10 mg twice daily is recommended, although in severely disturbed patients initial dosage up to a total of 50 mg daily may be desirable. Dosage should then be increased fairly rapidly over the first seven to ten days until there is effective control of symptoms of schizophrenia. The usual therapeutic and maintenance range is 60 mg to 100 mg daily. However, as with other drugs used to treat schizophrenia, some patients respond to lower dosage and others require higher dosage for optimal benefit. Daily dosage higher than 250 mg is not recommended.

Maintenance Therapy

For maintenance therapy, dosage should be reduced to the lowest level compatible with symptom control; many patients have been maintained satisfactorily at dosages in the range of 20 mg to 60 mg daily.

HOW SUPPLIED

Loxapine capsules, USP are available in the following strengths:

Loxapine succinate, USP 68.1 mg equivalent to 50 mg loxapine, black ink, hard shell, opaque, with a white body and blue cap, printed with “Watson 372” on one half and “50 mg” on the other, are supplied in

NDC: 70518-0416-00

NDC: 70518-0416-01

NDC: 70518-0416-02

PACKAGING: 30 in 1 BLISTER PACK

PACKAGING: 100 in 1 BOX

PACKAGING: 1 in 1 POUCH

Store at 20° to 25°C (68° to 77°F) [See USP Controlled Room Temperature]. Dispense in a tight, child-resistant container.

Repackaged and Distributed By:

Remedy Repack, Inc.

625 Kolter Dr. Suite #4 Indiana, PA 1-724-465-8762

PACKAGE LABEL

DRUG: Loxapine

GENERIC: Loxapine

DOSAGE: CAPSULE

ADMINSTRATION: ORAL

NDC: 70518-0416-0

NDC: 70518-0416-1
NDC: 70518-0416-2

COLOR: white

SHAPE: CAPSULE

SCORE: No score

SIZE: 19 mm

IMPRINT: Watson;372;50;mg

PACKAGING: 30 in 1 BLISTER PACK

PACKAGING: 100 in 1 BOX

PACKAGING: 1 in 1 POUCH

ACTIVE INGREDIENT(S):

- LOXAPINE SUCCINATE 50mg in 1

INACTIVE INGREDIENT(S):

- TITANIUM DIOXIDE
- SODIUM PROPIONATE
- SODIUM LAURYL SULFATE
- SHELLAC
- PROPYLPARABEN
- PROPYLENE GLYCOL
- POTASSIUM HYDROXIDE
- POLACRILIN POTASSIUM
- TALC
- METHYLPARABEN
- GELATIN
- FERROSOFERRIC OXIDE
- FD&C BLUE NO. 1
- EDETATE CALCIUM DISODIUM
- BUTYLPARABEN
- BENZYL ALCOHOL
- ANHYDROUS LACTOSE
- MAGNESIUM STEARATE
- AMMONIA